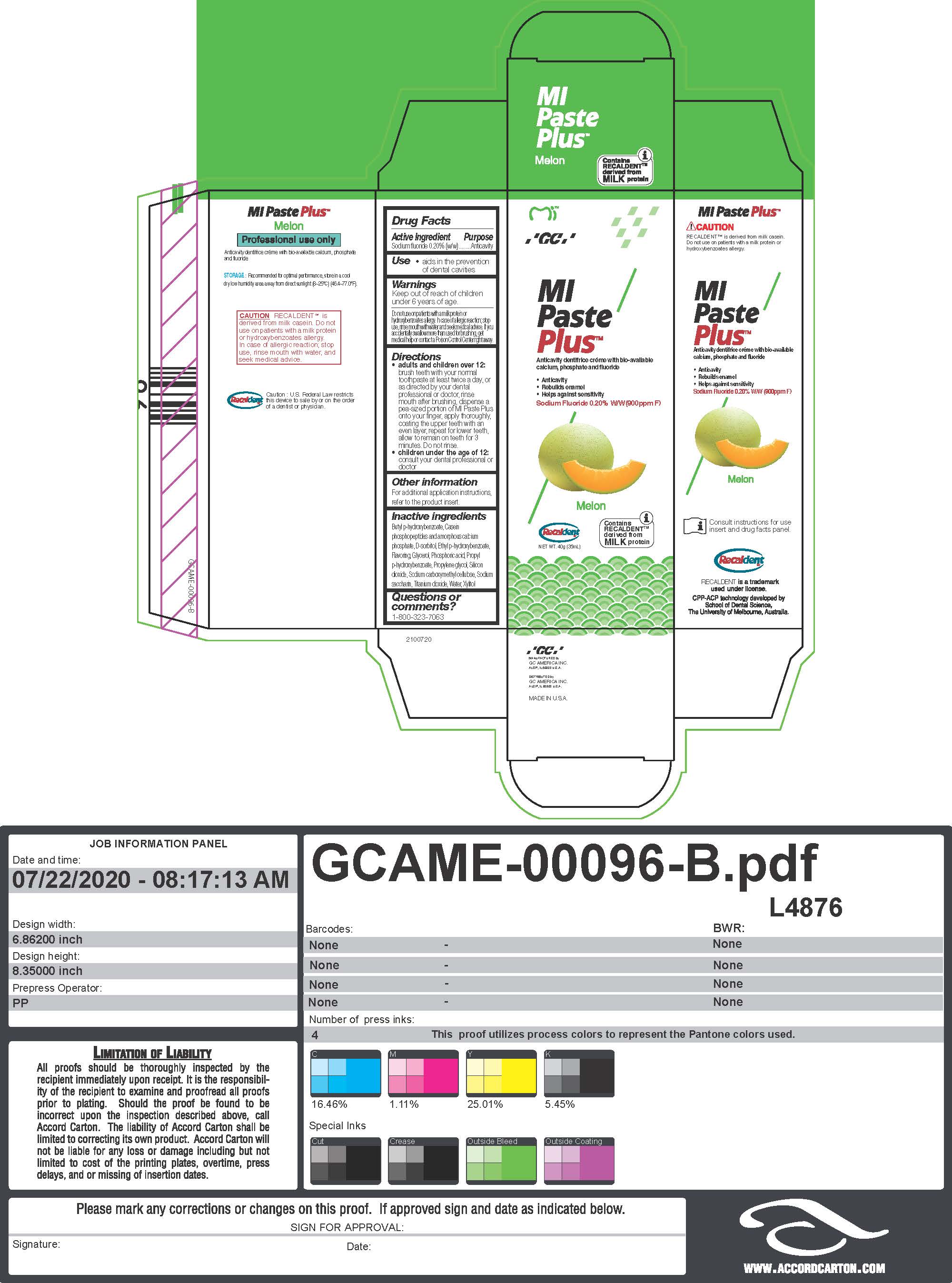 DRUG LABEL: MIPaste Plus Melon
NDC: 61596-804 | Form: PASTE, DENTIFRICE
Manufacturer: GC America Inc.
Category: otc | Type: HUMAN OTC DRUG LABEL
Date: 20251219

ACTIVE INGREDIENTS: SODIUM FLUORIDE 0.2 g/100 g
INACTIVE INGREDIENTS: BUTYLPARABEN; CALCIUM PHOSPHATE, UNSPECIFIED FORM; GLYCERIN; PHOSPHORIC ACID; CARBOXYMETHYLCELLULOSE SODIUM, UNSPECIFIED; TITANIUM DIOXIDE; PROPYLENE GLYCOL; WATER; XYLITOL; SACCHARIN SODIUM; SORBITOL; ETHYLPARABEN; PROPYLPARABEN; SILICON DIOXIDE

MIPaste Plus Melon

Active Ingredient
Sodium fluoride 0.20% (w/w)

Purpose
Anticavity

Use
• aids in the prevention
of dental cavities

Warnings
Keep out of reach of children under 6 years of age.
Do not use on patients with a milk protein or
hydroxybenzoates allergy. In case of allergic reaction; stop use, rinse mouth with water and seek medical advice. If you accidentally swallow more than used for brushing, get medical help or contact a Poison Control Center right away.

Warnings
Keep out of reach of children under 6 years of age.

Directions
• adults and children over 12:
brush teeth with your normal
toothpaste at least twice a day, or
as directed by your dental
professional or doctor, rinse
mouth after brushing, dispense a
pea-sized portion of MI Paste Plus
onto your finger, apply thoroughly,
coating the upper teeth with an
even layer, repeat for lower teeth,
allow to remain on teeth for 3
minutes. Do not rinse.
• children under the age of 12:
consult your dental professional or
doctor

Inactive ingredients
Butyl p-hydroxybenzoate, Casein
phosphopeptides and amorphous calcium
phosphate, D-sorbitol, Ethyl p-hydroxybenzoate,
Flavoring, Glycerol, Phosphoric acid, Propyl
p-hydroxybenzoate, Propylene glycol, Silicon
dioxide, Sodium carboxymethyl cellulose, Sodium
saccharin, Titanium dioxide, Water, Xylitol